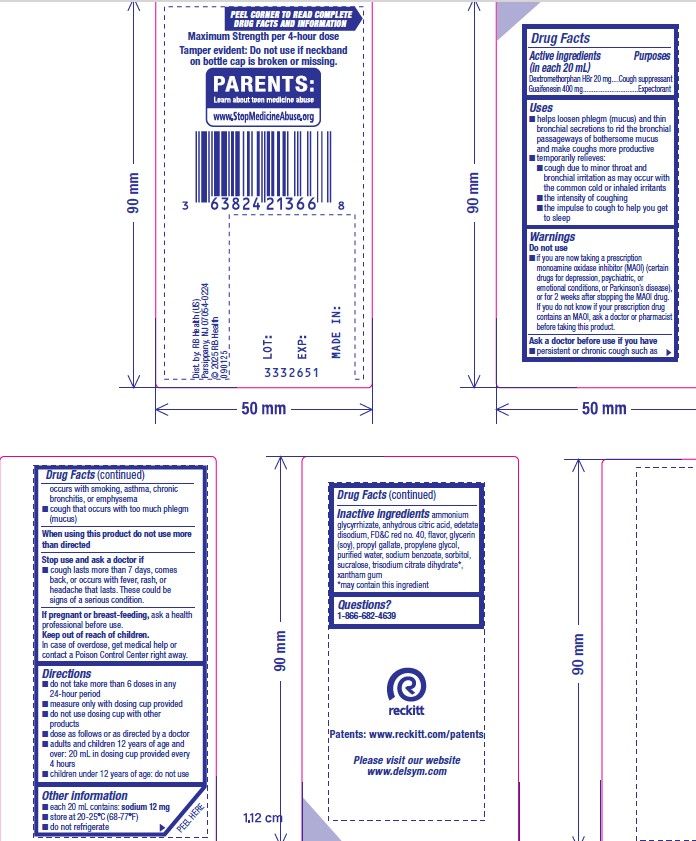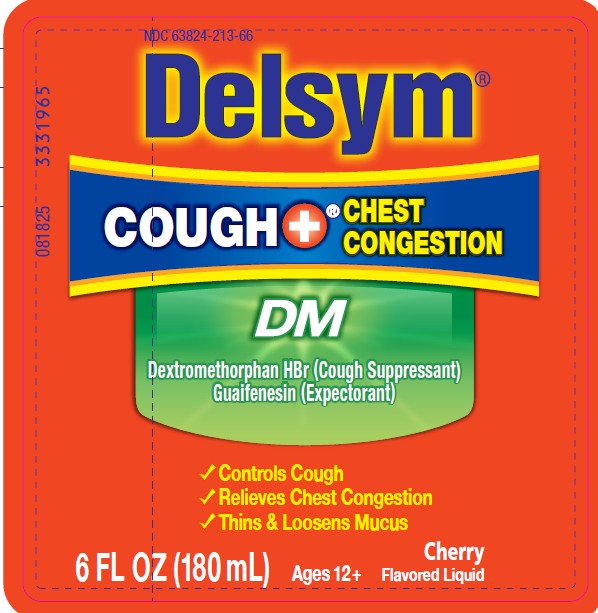 DRUG LABEL: Delsym
NDC: 63824-213 | Form: SOLUTION
Manufacturer: RB Health (US) LLC
Category: otc | Type: HUMAN OTC DRUG LABEL
Date: 20260223

ACTIVE INGREDIENTS: DEXTROMETHORPHAN HYDROBROMIDE 20 mg/20 mL; GUAIFENESIN 400 mg/20 mL
INACTIVE INGREDIENTS: AMMONIUM GLYCYRRHIZATE; EDETATE DISODIUM; FD&C RED NO. 40; ANHYDROUS CITRIC ACID; GLYCERIN; PROPYLENE GLYCOL; PROPYL GALLATE; WATER; SODIUM BENZOATE; SORBITOL; SUCRALOSE; TRISODIUM CITRATE DIHYDRATE; XANTHAN GUM

Delsym®
Cough Plus™ Chest Congestion DM

Drug Facts

ACTIVE INGREDIENT

PURPOSE

Active ingredients (in each 20 mL) | Purposes
Dextromethorphan HBr 20 mg | Cough suppressant
Guaifenesin 400 mg | Expectorant

Uses

- helps loosen phlegm (mucus) and thin bronchial secretions to rid the bronchial passageways of bothersome mucus and make coughs more productive
- temporarily relieves:
  - cough due to minor throat and bronchial irritation as may occur with the common cold or inhaled irritants
  - the intensity of coughing
  - the impulse to cough to help you get to sleep

Warnings

DO NOT USE

Do not useif you are now taking a prescription monoamine oxidase inhibitor (MAOI) (certain drugs for depression, psychiatric, or emotional conditions, or Parkinson's disease), or for 2 weeks after stopping the MAOI drug. If you do not know if your prescription drug contains an MAOI, ask a doctor or pharmacist before taking this product.

Ask a doctor before use if you have

- persistent or chronic cough such as occurs with smoking, asthma, chronic bronchitis, or emphysema
- cough that occurs with too much phlegm (mucus)

When using this product do not use more than directed

Stop use and ask a doctor if

- cough lasts more than 7 days, comes back, or occurs with fever, rash, or headache that lasts. These could be signs of a serious condition.

PREGNANCY OR BREAST FEEDING

If pregnant or breast-feeding,ask a health professional before use.

Keep out of reach of children.

In case of overdose, get medical help or contact a Poison Control Center right away.

Directions

- do not take more than 6 doses in any 24-hour period
- measure only with dosing cup provided
- do not use dosing cup with other products
- dose as follows or as directed by a doctor
- adults and children 12 years of age and over: 20 mL in dosing cup provided every 4 hours
- children under 12 years of age: do not use

Other information

- each 20 mL contains: sodium 12 mg
- store at 20-25°C (68-77°F)
- do not refrigerate

Inactive ingredients

ammonium glycyrrhizate, anhydrous citric acid, edetate disodium, FD&C red no. 40, flavor, glycerin(soy), propyl gallate, propylene glycol, purified water, sodium benzoate, sorbitol, sucralose, trisodium citrate dihydrate [may contain this ingredient] , xanthan gum

Questions?

1-866-682-4639

Dist. by: RB Health (US)
Parsippany, NJ 07054-0224

PRINCIPAL DISPLAY PANEL - 180 mL Bottle Label

NDC 63824-213-66

Delsym®

COUGH+™
CHEST
CONGESTION

DM

Dextromethorphan HBr (Cough Suppressant)
Guaifenesin (Expectorant)

- Controls Cough
- Relieves Chest Congestion
- Thins & Loosens Mucus

6 fl oz (180 mL)

For Ages 12+

Cherry
Flavored Liquid